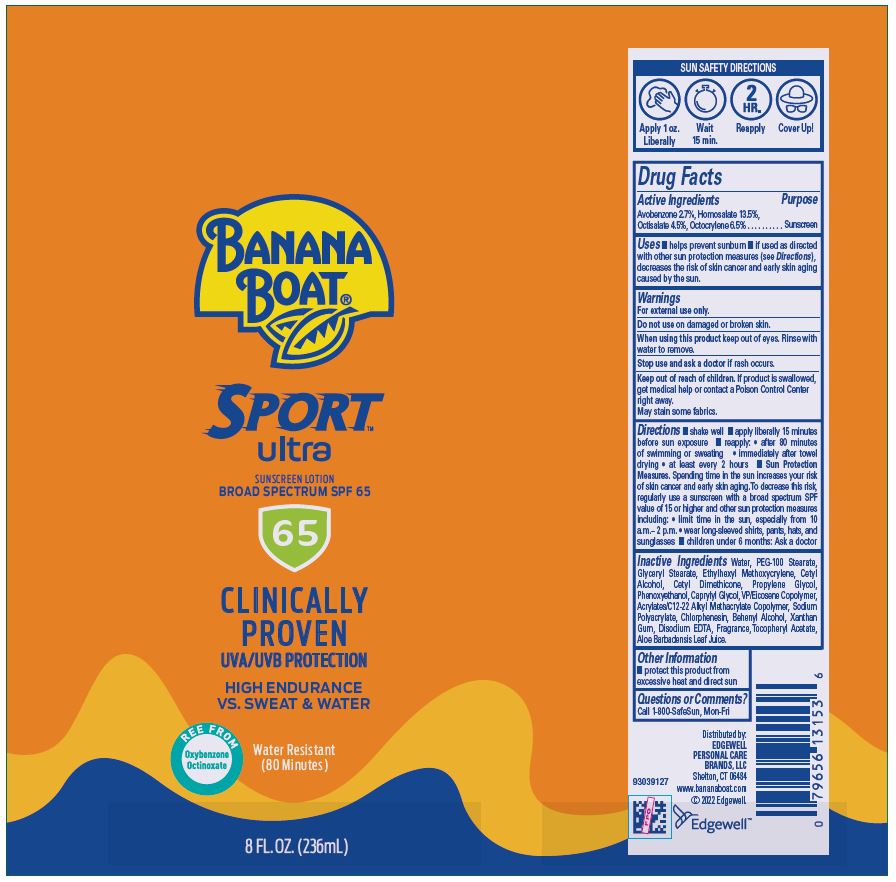 DRUG LABEL: Banana Boat Sport Ultra Sunscreen Broad Spectrum SPF 65
NDC: 63354-271 | Form: LOTION
Manufacturer: Edgewell Personal Care Brands LLC
Category: otc | Type: HUMAN OTC DRUG LABEL
Date: 20251202

ACTIVE INGREDIENTS: AVOBENZONE 2.7 g/100 g; OCTOCRYLENE 6.5 g/100 g; HOMOSALATE 13.5 g/100 g; OCTISALATE 4.5 g/100 g
INACTIVE INGREDIENTS: GLYCERYL 1-STEARATE; CETYL ALCOHOL; PROPYLENE GLYCOL; CAPRYLYL GLYCOL; CHLORPHENESIN; PEG-100 STEARATE; ETHYLHEXYL METHOXYCRYLENE; XANTHAN GUM; WATER; VINYLPYRROLIDONE/EICOSENE COPOLYMER; SODIUM POLYACRYLATE (2500000 MW); PHENOXYETHANOL; EDETATE DISODIUM; ALOE VERA LEAF; ALPHA-TOCOPHEROL ACETATE; DOCOSANOL

Active Ingredients

Avobenzone 2.7%, Homosalate 13.5%, Octisalate 4.5%, Octocrylene 6.5%

Purpose

Sunscreen

Uses

• helps prevent sunburn • if used as directed with other sun protection measures (see Directions), decreases the risk of skin cancer and early skin aging caused by the sun.

Warnings

For external use only.

May stain some fabrics.

Do not use

on damaged or broken skin.

When using this product

keep out of eyes. Rinse with water to remove.

Stop use and ask a doctor

if rash occurs.

Keep out of reach of children

If product is swallowed, get medical help or contact a Poison Control Center right away.

Directions

• shake well •apply liberally 15 minutes before sun exposure • reapply: • after 80 minutes of swimming or sweating • immediately after towel drying • at least every 2 hours • Sun Protection Measures. Spending time in the sun increases your risk of skin cancer and early skin aging. To decrease this risk, regularly use a sunscreen with a broad spectrum SPF value of 15 or higher and other sun protection measures including: • limit time in the sun, especially from 10 a.m.– 2 p.m. • wear long-sleeved shirts, pants, hats, and
sunglasses • children under 6 months: Ask a doctor

Inactive Ingredients

Water, PEG-100 Stearate, Glyceryl Stearate, Ethylhexyl Methoxycrylene, Cetyl Alcohol, Cetyl Dimethicone, Propylene Glycol, Phenoxyethanol, Caprylyl Glycol, VP/Eicosene Copolymer, Acrylates/C12-22 Alkyl Methacrylate Copolymer, Sodium Polyacrylate, Chlorphenesin, Behenyl Alcohol, Xanthan Gum, Disodium EDTA, Fragrance, Tocopheryl Acetate, Aloe Barbadensis Leaf Juice.

Other Information

- protect this product from excessive heat and direct sun

Questions or Comments?

Call 1-800-SafeSun, Mon-Fri

Princlipal Display Panel

BANANA
BOAT®
SPORT
ultra
SUNSCREEN LOTION
BROAD SPECTRUM SPF 65
65
CLINICALLY
PROVEN
UVA/UVB PROTECTION
HIGH ENDURANCE
VS. SWEAT & WATER
FREE FROM
Oxybenzone
Octinoxate
Water Resistant
(80 Minutes)
8 FL. OZ. (236mL)